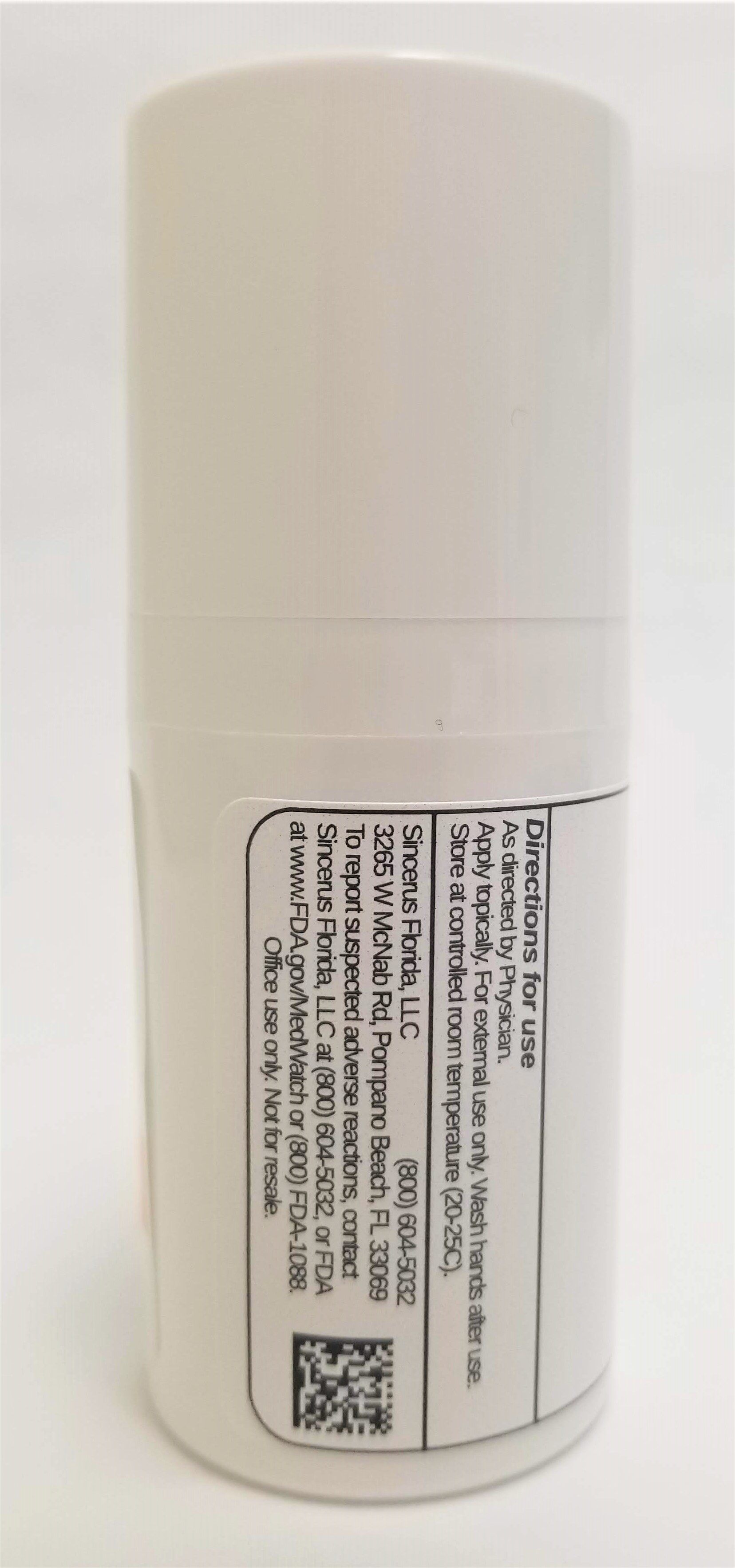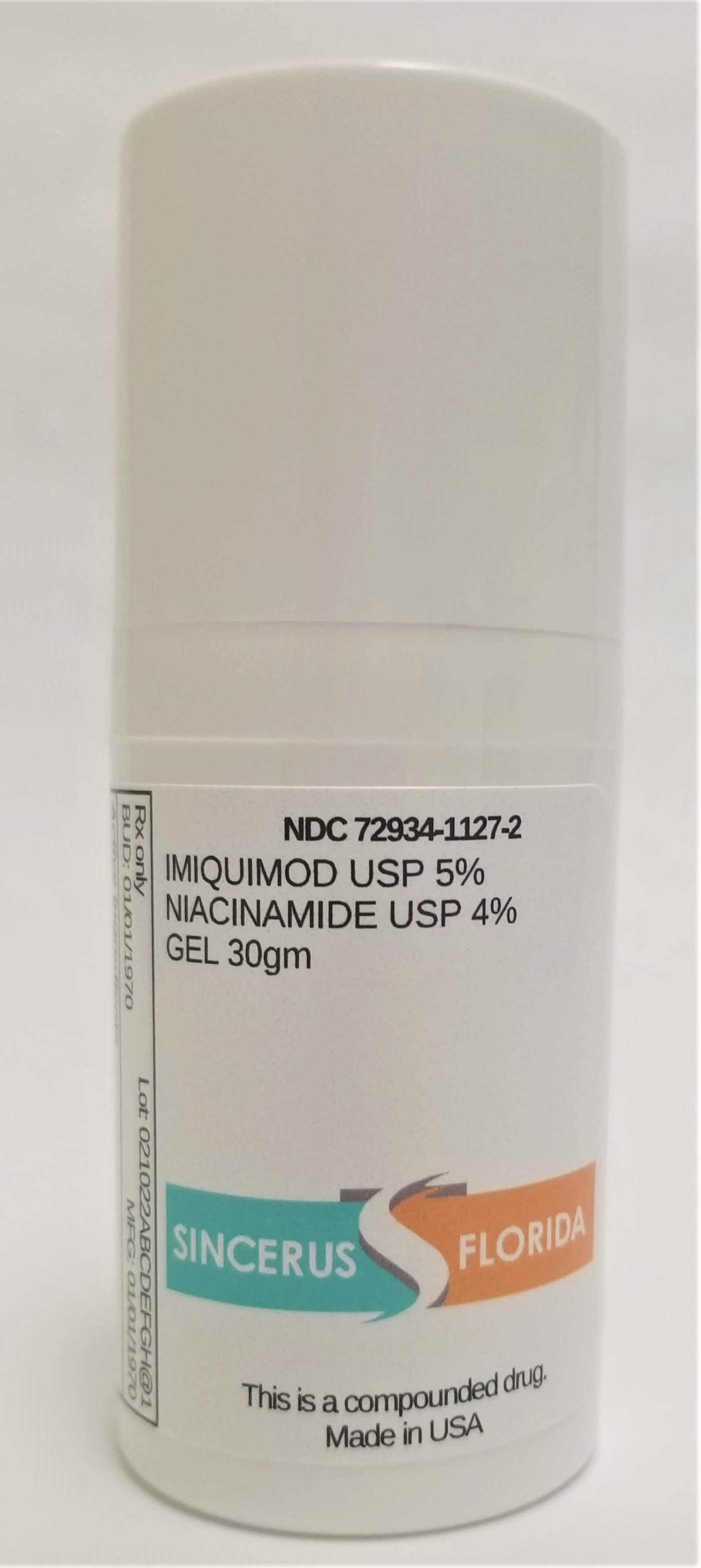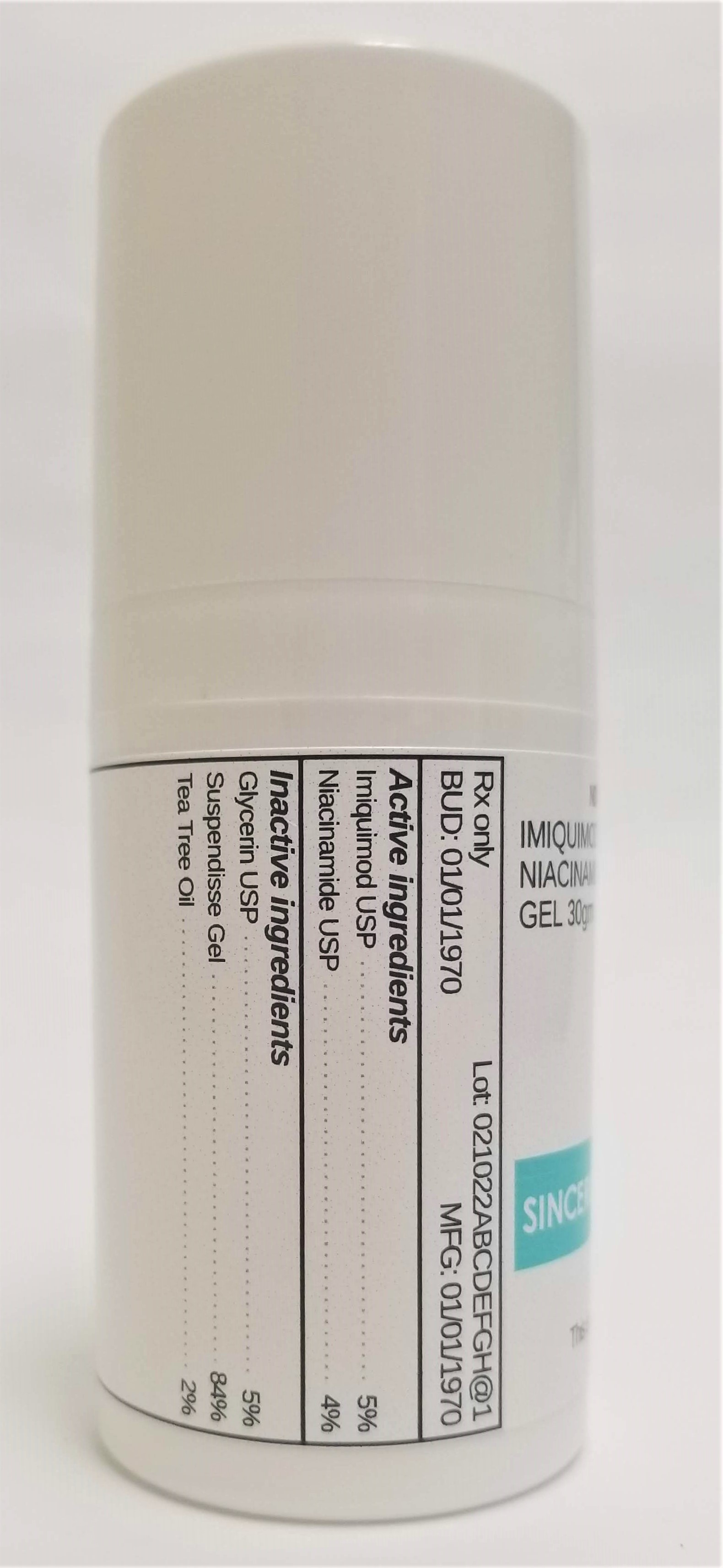 DRUG LABEL: IMIQUIMOD 5% / NIACINAMIDE 4%
NDC: 72934-1127 | Form: GEL
Manufacturer: Sincerus Florida, LLC
Category: prescription | Type: HUMAN PRESCRIPTION DRUG LABEL
Date: 20190506

ACTIVE INGREDIENTS: NIACINAMIDE 4 g/100 g; IMIQUIMOD 5 g/100 g

IMIQUIMOD 5% / NIACINAMIDE 4%